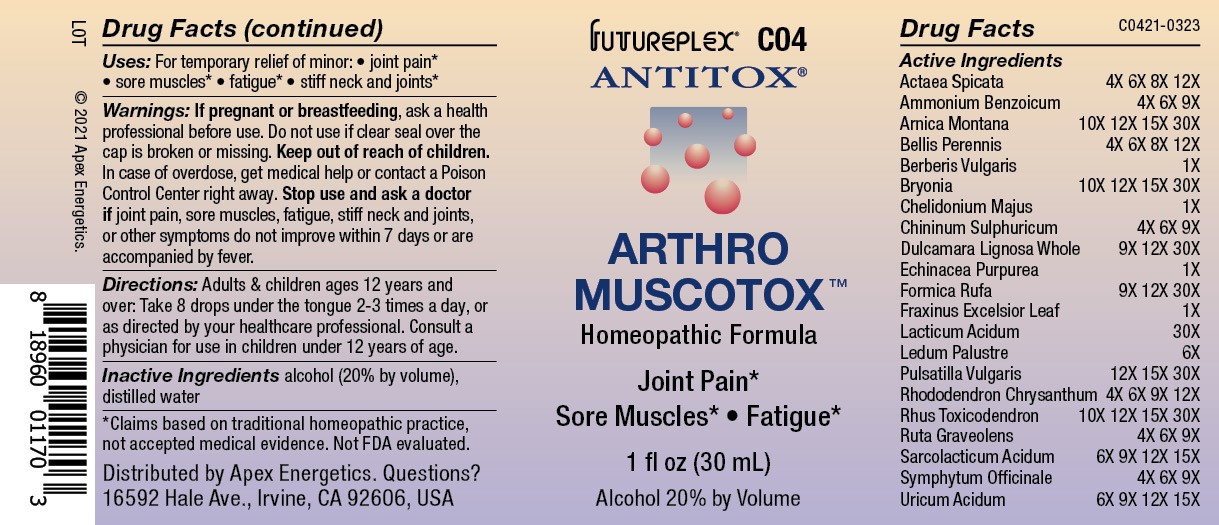 DRUG LABEL: C04
NDC: 63479-0304 | Form: SOLUTION/ DROPS
Manufacturer: Apex Energetics Inc.
Category: homeopathic | Type: HUMAN OTC DRUG LABEL
Date: 20240108

ACTIVE INGREDIENTS: SOLANUM DULCAMARA WHOLE 30 [hp_X]/1 mL; ECHINACEA PURPUREA 1 [hp_X]/1 mL; RUTA GRAVEOLENS FLOWERING TOP 9 [hp_X]/1 mL; ACTAEA SPICATA ROOT 12 [hp_X]/1 mL; FORMICA RUFA 30 [hp_X]/1 mL; FRAXINUS EXCELSIOR LEAF 1 [hp_X]/1 mL; LACTIC ACID, DL- 30 [hp_X]/1 mL; RHODODENDRON AUREUM LEAF 12 [hp_X]/1 mL; TOXICODENDRON PUBESCENS LEAF 30 [hp_X]/1 mL; PULSATILLA VULGARIS WHOLE 30 [hp_X]/1 mL; RHODODENDRON TOMENTOSUM LEAFY TWIG 6 [hp_X]/1 mL; AMMONIUM BENZOATE 9 [hp_X]/1 mL; ARNICA MONTANA 30 [hp_X]/1 mL; BERBERIS VULGARIS ROOT BARK 1 [hp_X]/1 mL; BRYONIA ALBA ROOT 30 [hp_X]/1 mL; LACTIC ACID, L- 15 [hp_X]/1 mL; COMFREY ROOT 9 [hp_X]/1 mL; URIC ACID 15 [hp_X]/1 mL; BELLIS PERENNIS 12 [hp_X]/1 mL; CHELIDONIUM MAJUS 1 [hp_X]/1 mL; QUININE SULFATE 9 [hp_X]/1 mL
INACTIVE INGREDIENTS: ALCOHOL; WATER

C04

Active Ingredients
Actaea Spicata | 4X 6X 8X 12X
Ammonium Benzoicum | 4X 6X 9X
Arnica Montana | 10X 12X 15X 30X
Bellis Perennis | 4X 6X 8X 12X
Berberis Vulgaris | 1X
Bryonia | 10X 12X 15X 30X
Chelidonium Majus | 1X
Chininum Sulphuricum | 4X 6X 9X
Dulcamara Lignosa Whole | 9X 12X 30X
Echinacea Purpurea | 1X
Formica Rufa | 9X 12X 30X
Fraxinus Excelsior Leaf | 1X
Lacticum Acidum | 30X
Ledum Palustre | 6X
Pulsatilla Vulgaris | 12X 15X 30X
Rhododendron Chrysanthum | 4X 6X 9X 12X
Rhus Toxicodendron | 10X 12X 15X 30X
Ruta Graveolens | 4X 6X 9X
Sarcolacticum Acidum | 6X 9X 12X 15X
Symphytum Officinale | 4X 6X 9X
Uricum Acidum | 6X 9X 12X 15X

INDICATIONS AND USAGE

Uses:

For temporary relief of minor:

joint pain*

sore muscles*

fatigue*

stiff neck and joints*

*Claims based on traditional homeopathic practice, not accepted medical evidence. Not FDA evaluated.

Warnings:

PREGNANCY OR BREAST FEEDING

If pregnant or breastfeeding, ask a health professional before use.

Do not use if clear seal over the cap is broken or missing.

Keep out of reach of children. In case of overdose, get medical help or contact a Poison Control Center right away.

Stop use and ask a doctor if joint pain, sore muscles, fatigue, stiff neck and joints, or other symptoms do not improve within 7 days or are accompanied by fever.

Directions:

Adults & children ages 12 years and over: Take 8 drops under the tongue 2-3 times a day, or as directed by your healthcare professional. Consult a physician for use in children under 12 years of age.

Inactive Ingredients

alcohol (20% by volume), distilled water

Distributed by Apex Energetics. Questions?

16592 Hale Ave., Irvine, CA 92606, USA

PACKAGE LABEL

FUTUREPLEX® C04

ANTITOX®

ARTHRO MUSCOTOX™

Homeopathic Formula

Joint Pain*

Sore Muscles*

Fatigue*

1 fl oz (30 mL)

Alcohol 20% by Volume